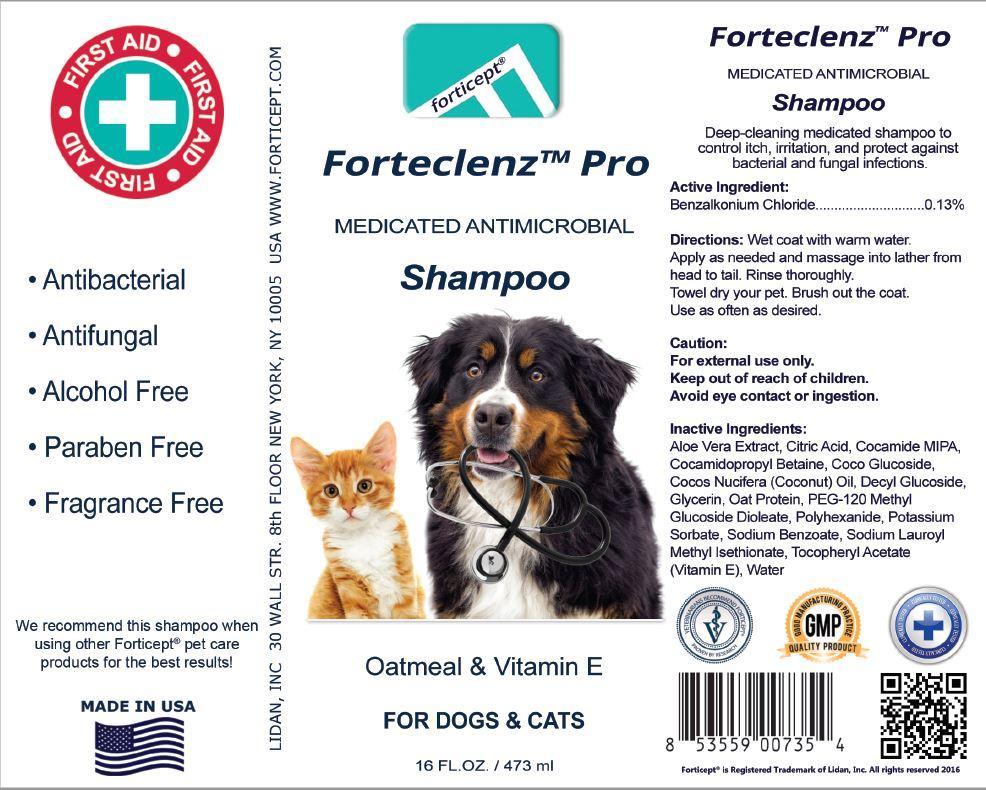 DRUG LABEL: Forticept Forteclenz Pro
NDC: 72127-0707 | Form: LIQUID
Manufacturer: Lidan, Inc.
Category: animal | Type: OTC ANIMAL DRUG LABEL
Date: 20240927

ACTIVE INGREDIENTS: BENZALKONIUM CHLORIDE 0.013 kg/1 kg

FORTICEPT FORTECLENZ PRO ANTIMICROBIAL SHAMPOO

Active Ingredient:

Benzalkonium Chloride ................ 0.13%

Active Ingredient:

Benzalkonium Chloride ................ 0.13%

Active Ingredient:

Benzalkonium Chloride ................ 0.13%

Description:

Deep-cleaning medicated shampoo to control itch, irritation, and protect against bacterial and fungal infections

Uses:

For use on dogs, cats, and horses as an aid in the control of common skin conditions: ringworm, summer itch, girth itch, pyoderma, and other bacterial or fungal infections.

Caution:

For external use only Keep out of reach of children Avoid eye contact or ingestion

Inactive Ingredients:

Aloe Vera Extract, Citric Acid, Cocamide MIPA, Cocamidopropyl Betaine, Coco Glucoside, Coconut Oil, Decyl Glucoside, Glycerin, Oat Protein, PEG-120 Methyl Glucoside Dioleate, Polyhexanide, Potassium Sorbate, Sodium Benzoate, Sodium Lauroyl Methyl Isethionate, Tocopheryl Acetate (Vitamin E), Water